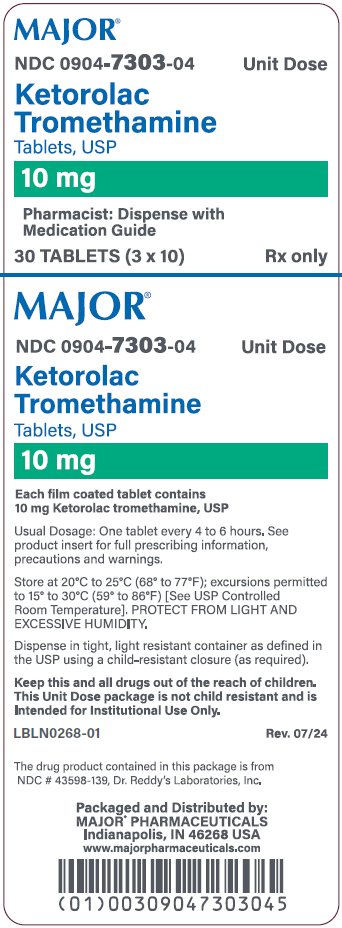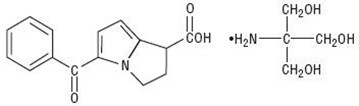 DRUG LABEL: Ketorolac Tromethamine
NDC: 0904-7303 | Form: TABLET, FILM COATED
Manufacturer: Major Pharmaceuticals
Category: prescription | Type: HUMAN PRESCRIPTION DRUG LABEL
Date: 20260219

ACTIVE INGREDIENTS: KETOROLAC TROMETHAMINE 10 mg/1 1
INACTIVE INGREDIENTS: LACTOSE MONOHYDRATE; MAGNESIUM STEARATE; MICROCRYSTALLINE CELLULOSE; HYPROMELLOSE 2910 (6 MPA.S); POLYETHYLENE GLYCOL 400; TITANIUM DIOXIDE

Ketorolac Tromethamine Tablets, USP 10mg

BOXED WARNING

Ketorolac tromethamine tablets, a nonsteroidal anti-inflammatory drug (NSAID), are indicated for the short-term (up to 5 days in adults), management of moderately severe acute pain that requires analgesia at the opioid level and only as continuation treatment following IV or IM dosing of ketorolac tromethamine, if necessary. The total combined duration of use of ketorolac tromethamine tablets and ketorolac tromethamine should not exceed 5 days.

Ketorolac tromethamine tablets are not indicated for use in pediatric patients and they are NOT indicated for minor or chronic painful conditions. Increasing the dose of ketorolac tromethamine tablets beyond a daily maximum of 40 mg in adults will not provide better efficacy but will increase the risk of developing serious adverse events.

GASTROINTESTINAL RISK

- Ketorolac tromethamine, including ketorolac tromethamine tablets can cause peptic ulcers, gastrointestinal bleeding and/or perforation of the stomach or intestines, which can be fatal. These events can occur at any time during use and without warning symptoms. Therefore, ketorolac tromethamine is CONTRAINDICATED in patients with active peptic ulcer disease, in patients with recent gastrointestinal bleeding or perforation, and in patients with a history of peptic ulcer disease or gastrointestinal bleeding. Elderly patients are at greater risk for serious gastrointestinal events (see WARNINGS).

CARDIOVASCULAR THOMBOTIC EVENTS

- Nonsteroidal anti-inflammatory drugs (NSAIDs) cause an increased risk of serious cardiovascular thrombotic events, including myocardial infarction and stroke, which can be fatal. This risk may occur early in treatment and may increase with duration of use (see WARNINGS and PRECAUTIONS).
- Ketorolac tromethamine tablets are contraindicated in the setting of coronary artery bypass graft (CABG) surgery (see CONTRAINDICATIONS and WARNINGS).

RENAL RISK

- Ketorolac tromethamine is CONTRAINDICATED in patients with advanced renal impairment and in patients at risk for renal failure due to volume depletion (see WARNINGS).

RISK OF BLEEDING

- Ketorolac tromethamine inhibits platelet function and is, therefore, CONTRAINDICATED in patients with suspected or confirmed cerebrovascular bleeding, patients with hemorrhagic diathesis, incomplete hemostasis and those at high risk of bleeding (see WARNINGS and PRECAUTIONS).

Ketorolac tromethamine is CONTRAINDICATED as prophylactic analgesic before any major surgery.

RISK DURING LABOR AND DELIVERY

- The use of ketorolac tromethamine in labor and delivery is contraindicated because it may adversely affect fetal circulation and inhibit uterine contractions.

CONCOMITANT USE WITH NSAIDs

- Ketorolac tromethamine is CONTRAINDICATED in patients currently receiving aspirin or NSAIDs because of the cumulative risk of inducing serious NSAID-related side effects.

SPECIAL POPULATIONS

- Dosage should be adjusted for patients 65 years or older, for patients under 50 kg (110 lbs) of body weight (see DOSAGE AND ADMINISTRATION) and for patients with moderately elevated serum creatinine (see WARNINGS).

DESCRIPTION

Ketorolac Tromethamine Tablets, USP are a member of the pyrrolo-pyrrole group of nonsteroidal anti- inflammatory drugs (NSAIDs). The chemical name for ketorolac tromethamine, USP is (±)-5-benzoyl- 2,3-dihydro-1H-pyrrolizine-1-carboxylic acid, compound with 2-amino-2-(hydroxymethyl)-1,3- propanediol (1:1). The structural formula is:

C15H13NO3.C4H11NO3 M.W. 376.40

Ketorolac tromethamine, USP is a racemic mixture of [-]S and [+]R ketorolac tromethamine, USP. Ketorolac tromethamine, USP may exist in three crystal forms. All forms are equally soluble in water. Ketorolac tromethamine, USP has a pKa of 3.5 and an n-octanol/water partition coefficient of 0.26.

Ketorolac Tromethamine Tablets, USP are white, round, convex, unscored, film-coated tablets. Each tablet, for oral administration, contains 10 mg ketorolac tromethamine, USP, the active ingredient. In addition, each tablet contains the following inactive ingredients: lactose monohydrate, magnesium stearate, microcrystalline cellulose, hypromellose 2910 (6 mpa.s), polyethylene glycol 400 and titanium dioxide.

CLINICAL PHARMACOLOGY

Pharmacodynamics

Ketorolac tromethamine is a nonsteroidal anti-inflammatory drug (NSAID) that exhibits analgesic activity in animal models. The mechanism of action of ketorolac, like that of other NSAIDs, is not completely understood but may be related to prostaglandin synthetase inhibition. The biological activity of ketorolac tromethamine is associated with the S-form. Ketorolac tromethamine possesses no sedative or anxiolytic properties.

The peak analgesic effect of ketorolac tromethamine occurs within 2 to 3 hours and is not statistically significantly different over the recommended dosage range of ketorolac tromethamine. The greatest difference between large and small doses of ketorolac tromethamine is in the duration of analgesia.

Pharmacokinetics

Ketorolac tromethamine is a racemic mixture of [-]S- and [+]R-enantiomeric forms, with the S-form having analgesic activity.

Comparison of IV, IM and Oral Pharmacokinetics

The pharmacokinetics of ketorolac tromethamine, following IV and IM doses of ketorolac tromethamine and oral doses of ketorolac tromethamine, are compared in Table 1. In adults, the extent of bioavailability following administration of the ORAL form of ketorolac tromethamine and the IM form of ketorolac tromethamine was equal to that following an IV bolus.

Linear Kinetics

In adults, following administration of single ORAL doses of ketorolac tromethamine or IM or IV doses of ketorolac tromethamine in the recommended dosage ranges, the clearance of the racemate does not change. This implies that the pharmacokinetics of ketorolac tromethamine in adults, following single or multiple IM or IV doses of ketorolac tromethamine or recommended oral doses of ketorolac tromethamine, are linear. At the higher recommended doses, there is a proportional increase in the concentrations of free and bound racemate.

Absorption

Ketorolac tromethamine is 100% absorbed after oral administration (see Table 1). Oral administration of ketorolac tromethamine after a high-fat meal resulted in decreased peak and delayed time-to-peak concentrations of ketorolac tromethamine by about 1 hour. Antacids did not affect the extent of absorption.

Distribution

The mean apparent volume (Vß) of ketorolac tromethamine following complete distribution was approximately 13 liters. This parameter was determined from single-dose data. The ketorolac tromethamine racemate has been shown to be highly protein bound (99%). Nevertheless, plasma concentrations as high as 10 mcg/mL will only occupy approximately 5% of the albumin binding sites. Thus, the unbound fraction for each enantiomer will be constant over the therapeutic range. A decrease in serum albumin, however, will result in increased free drug concentrations.

Ketorolac tromethamine is excreted in human milk (see PRECAUTIONS, Nursing Mothers).

Metabolism

Ketorolac tromethamine is largely metabolized in the liver. The metabolic products are hydroxylated and conjugated forms of the parent drug. The products of metabolism, and some unchanged drug, are excreted in the urine.

Excretion

The principal route of elimination of ketorolac and its metabolites is renal. About 92% of a given dose is found in the urine, approximately 40% as metabolites and 60% as unchanged ketorolac.

Approximately 6% of a dose is excreted in the feces. A single-dose study with 10 mg ketorolac tromethamine (n = 9) demonstrated that the S-enantiomer is cleared approximately two times faster than the R-enantiomer and that the clearance was independent of the route of administration. This means that the ratio of S/R plasma concentrations decreases with time after each dose. There is little or no inversion of the R- to S- form in humans. The clearance of the racemate in normal subjects, elderly individuals and in hepatically and renally impaired patients is outlined in Table 2 (see CLINICAL PHARMACOLOGY, Kinetics in Special Populations).

The half-life of the ketorolac tromethamine S-enantiomer was approximately 2.5 hours (SD ± 0.4) compared with 5 hours (SD ± 1.7) for the R-enantiomer. In other studies, the half-life for the racemate has been reported to lie within the range of 5 to 6 hours.

Accumulation

Ketorolac tromethamine administered as an IV bolus every 6 hours for 5 days to healthy subjects (n = 13), showed no significant difference in Cmax on Day 1 and Day 5. Trough levels averaged 0.29 mcg/mL (SD ± 0.13) on Day 1 and 0.55 mcg/mL (SD ± 0.23) on Day 6. Steady state was approached after the fourth dose.

Accumulation of ketorolac tromethamine has not been studied in special populations (geriatric, pediatric, renal failure or hepatic disease patients).

Kinetics in Special Populations

Geriatric Patients

Based on single-dose data only, the half-life of the ketorolac tromethamine racemate increased from 5 to 7 hours in the elderly (65 to 78 years) compared with young healthy volunteers (24 to 35 years) (see Table 2). There was little difference in the Cmax for the two groups (elderly, 2.52 mcg/mL ± 0.77; young, 2.99 mcg/mL ± 1.03) (see PRECAUTIONS, Geriatric Use (≥ 65 Years of Age)).

Pediatric Patients

Limited information is available regarding the pharmacokinetics of dosing of ketorolac tromethamine in the pediatric population. Following a single intravenous bolus dose of 0.5 mg/kg in 10 children 4 to 8 years old, the half-life was 5.8 ± 1.6 hours, the average clearance was 0.042 ± 0.01 L/hr/kg, the volume of distribution during the terminal phase (Vβ) was 0.34 ± 0.12 L/kg and the volume of distribution at steady state (Vss) was 0.26 ± 0.08 L/kg. The volume of distribution and clearance of ketorolac in pediatric patients was higher than those observed in adult subjects (see Table 1). There are no pharmacokinetic data available for administration of ketorolac tromethamine by the IM route in pediatric patients.

Renal Insufficiency

Based on single-dose data only, the mean half-life of ketorolac tromethamine in renally impaired patients is between 6 and 19 hours and is dependent on the extent of the impairment. There is poor correlation between creatinine clearance and total ketorolac tromethamine clearance in the elderly and populations with renal impairment (r =0.5).

In patients with renal disease, the AUC∞ of each enantiomer increased by approximately 100% compared with healthy volunteers. The volume of distribution doubles for the S-enantiomer and increases by 1/5th for the R-enantiomer. The increase in volume of distribution of ketorolac tromethamine implies an increase in unbound fraction.

The AUC∞-ratio of the ketorolac tromethamine enantiomers in healthy subjects and patients remained similar, indicating there was no selective excretion of either enantiomer in patients compared to healthy subjects (see WARNINGS, Renal Effects).

Hepatic Insufficiency

There was no significant difference in estimates of half-life, AUC∞ and Cmax in 7 patients with liver disease compared to healthy volunteers (see PRECAUTIONS, Hepatic Effect and Table 2).

Race

Pharmacokinetic differences due to race have not been identified.

Table 1: Table of Approximate Average Pharmacokinetic Parameters (Mean ± SD) Following Oral, Intramuscular and Intravenous Doses of Ketorolac Tromethamine
Pharmacokinetic Parameters (units) | Oral [Derived from PO pharmacokinetic studies in 77 normal fasted volunteers] | Intramuscular [Derived from IM pharmacokinetic studies in 54 normal volunteers] |  |  | Intravenous Bolus [Derived from IV pharmacokinetic studies in 24 normal volunteers]
 | 10 mg | 15 mg | 30 mg | 60 mg | 15 mg | 30 mg
Bioavailability (extent) | 100%
Tmax [Time to peak plasma concentration] (min) | 44 ± 34 | 33 ± 21 [Mean value was simulated from observed plasma concentration data and standard deviation was simulated from percent coefficient of variation for observed Cmax and Tmax data] | 44 ± 29 | 33 ± 21 | 1.1 ± 0.74 | 2.9 ± 1.8
Cmax [Peak plasma concentration] (mcg/mL) [single-dose] | 0.87 ± 0.22 | 1.14 ± 0.32 | 2.42 ± 0.68 | 4.55 ± 1.27 | 2.47 ± 0.51 | 4.65 ± 0.96
Cmax (mcg/mL) [steady state qid] | 1.05 ± 0.26 | 1.56 ± 0.44 | 3.11 ± 0.87 | N/A [Not applicable because 60 mg is only recommended as a single dose] | 3.09 ± 1.17 | 6.85 ± 2.61
Cmin [Trough plasma concentration] (mcg/mL) [steady state qid] | 0.29 ± 0.07 | 0.47 ± 0.13 | 0.93 ± 0.26 | N/A | 0.61 ± 0.21 | 1.04 ± 0.35
Cavg [Average plasma concentration] (mcg/mL) [steady state qid] | 0.59 ± 0.20 | 0.94 ± 0.29 | 1.88 ± 0.59 | N/A | 1.09 ± 0.30 | 2.17 ± 0.59
Vβ [Volume of distribution] (L/kg) | 0.175 ± 0.039 |  |  |  |  | 0.210 ± 0.04
% Dose metabolized ≤ 50 |  |  | % Dose excreted in feces =6
% Dose excreted in urine = 91 |  |  | % Plasma protein binding = 99

Table 2: The Influence of Age, Liver, and Kidney Function on the Clearance and Terminal Half- Life of Ketorolac Tromethamine (IM [Estimated from 30 mg single IM doses of ketorolac tromethamine] and ORAL [Estimated from 10 mg single oral doses of ketorolac tromethamine]) in Adult Populations
 | Total Clearance [in L/h/kg] [Liters/hour/kilogram] |  | Terminal Half-Life [in hours]
Type of Subjects | IM | ORAL | IM | ORAL
Type of Subjects | Mean (range) | Mean (range) | Mean (range) | Mean (range)
Normal Subjects IM (n = 54) mean age = 32, range = 18 to 60 Oral (n = 77) mean age = 32, range = 20 to 60 | 0.023 | 0.025 | 5.3 | 5.3
Normal Subjects IM (n = 54) mean age = 32, range = 18 to 60 Oral (n = 77) mean age = 32, range = 20 to 60 | (0.010 to 0.046) | (0.013 to 0.050) | (3.5 to 9.2) | (2.4 to 9)
Healthy Elderly Subjects IM (n = 13), Oral (n = 12) mean age = 72, range = 65 to 78 | 0.019 | 0.024 | 7 | 6.1
Healthy Elderly Subjects IM (n = 13), Oral (n = 12) mean age = 72, range = 65 to 78 | (0.013 to 0.034) | (0.018 to 0.034) | (4.7 to 8.6) | (4.3 to 7.6)
Patients With Hepatic Dysfunction IM and Oral (n = 7) mean age = 51, range = 43 to 64 | 0.029 | 0.033 | 5.4 | 4.5
Patients With Hepatic Dysfunction IM and Oral (n = 7) mean age = 51, range = 43 to 64 | (0.013 to 0.066) | (0.019 to 0.051) | (2.2 to 6.9) | (1.6 to 7.6)
Patients With Renal Impairment IM (n = 25), Oral (n = 9) serum creatinine = 1.9 to 5 mg/dL, mean age (IM) = 54, range = 35 to 71 mean age (Oral) = 57, range = 39 to 70 | 0.015 | 0.016 | 10.3 | 10.8
Patients With Renal Impairment IM (n = 25), Oral (n = 9) serum creatinine = 1.9 to 5 mg/dL, mean age (IM) = 54, range = 35 to 71 mean age (Oral) = 57, range = 39 to 70 | (0.005 to 0.043) | (0.007 to 0.052) | (5.9 to 19.2) | (3.4 to 18.9)
Renal Dialysis Patients IM and Oral (n = 9) Caption: mean age = 40, range = 27 to 63 | 0.016 | -- | 13.6 | --
Renal Dialysis Patients IM and Oral (n = 9) Caption: mean age = 40, range = 27 to 63 | (0.003 to 0.036) | (8 to 39.1)

IV Administration

In normal adult subjects (n = 37), the total clearance of 30 mg IV-administered ketorolac tromethamine was 0.030 (0.017 to 0.051) L/h/kg. The terminal half-life was 5.6 (4 to 7.9) hours (see Kinetics in Special Populations for use of IV dosing of ketorolac tromethamine in pediatric patients).

CLINICAL STUDIES

Adult Patients

In a postoperative study, where all patients received morphine by a PCA device, patients treated with ketorolac tromethamine IV as fixed intermittent boluses (e.g., 30 mg initial dose followed by 15 mg q3h), required significantly less morphine (26%) than the placebo group. Analgesia was significantly superior, at various postdosing pain assessment times, in the patients receiving ketorolac tromethamineIV plus PCA morphine as compared to patients receiving PCA-administered morphine alone.

Pediatric Patients

There are no data available to support the use of ketorolac tromethamine tablets in pediatric patients.

INDICATIONS AND USAGE

Carefully consider the potential benefits and risks of Ketorolac Tromethamine Tablets USP and other treatment options before deciding to use Ketorolac Tromethamine Tablets USP. Use the lowest effective dose for the shortest duration consistent with individual patient treatment goals.

Acute Pain in Adult Patients

Ketorolac Tromethamine Tablets USP are indicated for the short-term (≤ 5 days) management of moderately severe acute pain that requires analgesia at the opioid level, usually in a postoperative setting. Therapy should always be initiated with IV or IM dosing of ketorolac tromethamine and Ketorolac Tromethamine Tablets USP are to be used only as continuation treatment, if necessary.

The total combined duration of use of Ketorolac Tromethamine Tablets USP and ketorolac tromethamine is not to exceed 5 days of use because of the potential of increasing the frequency and severity of adverse reactions associated with the recommended doses (see WARNINGS, PRECAUTIONS, DOSAGE AND ADMINISTRATION, and ADVERSE REACTIONS). Patients should be switched to alternative analgesics as soon as possible, but Ketorolac Tromethamine Tablet USP therapy is not to exceed 5 days.

CONTRAINDICATIONS

(See also Boxed WARNING.)

Ketorolac tromethamine is contraindicated in patients with previously demonstrated hypersensitivity to ketorolac tromethamine.

Ketorolac tromethamine is contraindicated in patients with active peptic ulcer disease, in patients with recent gastrointestinal bleeding or perforation and in patients with a history of peptic ulcer disease or gastrointestinal bleeding.

Ketorolac tromethamine should not be given to patients who have experienced asthma, urticaria, or allergic-type reactions after taking aspirin or other NSAIDs. Severe, rarely fatal, anaphylactic-like reactions to NSAIDs have been reported in such patients (see WARNINGS, Anaphylactoid Reactions and PRECAUTIONS, Preexisting Asthma)

Ketorolac tromethamine is contraindicated as prophylactic analgesic before any major surgery.

Ketorolac tromethamine is contraindicated in the setting of coronary artery bypass graft (CABG) surgery (see WARNINGS).

Ketorolac tromethamine is contraindicated in patients with advanced renal impairment or in patients at risk for renal failure due to volume depletion (see WARNINGS for correction of volume depletion).

Ketorolac tromethamine is contraindicated in labor and delivery because, through its prostaglandin synthesis inhibitory effect, it may adversely affect fetal circulation and inhibit uterine contractions, thus increasing the risk of uterine hemorrhage.

Ketorolac tromethamine inhibits platelet function and is, therefore, contraindicated in patients with suspected or confirmed cerebrovascular bleeding, hemorrhagic diathesis, incomplete hemostasis and those at high risk of bleeding (see WARNINGS and PRECAUTIONS).

Ketorolac tromethamine is contraindicated in patients currently receiving aspirin or NSAIDs because of the cumulative risks of inducing serious NSAID-related adverse events.

The concomitant use of ketorolac tromethamine and probenecid is contraindicated. The concomitant use of ketorolac tromethamine and pentoxifylline is contraindicated.

WARNINGS

(See also Boxed WARNING.)

The total combined duration of use of ketorolac tromethamine tablets and IV or IM dosing of ketorolac tromethamine is not to exceed 5 days in adults. Ketorolac tromethamine tablets are not indicated for use in pediatric patients.

The most serious risks associated with ketorolac tromethamine are:

Gastrointestinal Effects – Risk of Ulceration, Bleeding, and Perforation

Ketorolac tromethamine is contraindicated in patients with previously documented peptic ulcers and/or GI bleeding. Ketorolac tromethamine can cause serious gastrointestinal (GI) adverse events including bleeding, ulceration and perforation, of the stomach, small intestine, or large intestine, which can be fatal. These serious adverse events can occur at any time, with or without warning symptoms, in patients treated with ketorolac tromethamine.

Only one in five patients who develop a serious upper GI adverse event on NSAID therapy is symptomatic. Minor upper gastrointestinal problems, such as dyspepsia, are common and may also occur at any time during NSAID therapy. The incidence and severity of gastrointestinal complications increases with increasing dose of, and duration of treatment with, ketorolac tromethamine. Do not use ketorolac tromethamine for more than five days. However, even short-term therapy is not without risk. In addition to past history of ulcer disease, other factors that increase the risk for GI bleeding in patients treated with NSAIDs include concomitant use of oral corticosteroids, or anticoagulants, longer duration of NSAID therapy, smoking, use of alcohol, older age, and poor general health status. Most spontaneous reports of fatal GI events are in elderly or debilitated patients and therefore, special care should be taken in treating this population.

To minimize the potential risk for an adverse GI event, the lowest effective dose should be used for the shortest possible duration. Patients and physicians should remain alert for signs and symptoms of GI ulceration and bleeding during NSAID therapy and promptly initiate additional evaluation and treatment if a serious GI adverse event is suspected. This should include discontinuation of ketorolac tromethamine until a serious GI adverse event is ruled out. For high risk patients, alternate therapies that do not involve NSAIDs should be considered.

NSAIDs should be given with care to patients with a history of inflammatory bowel disease (ulcerative colitis, Crohn's disease) as their condition may be exacerbated.

Hemorrhage

Because prostaglandins play an important role in hemostasis and NSAIDs affect platelet aggregation as well, use of ketorolac tromethamine in patients who have coagulation disorders should be undertaken very cautiously, and those patients should be carefully monitored. Patients on therapeutic doses of anticoagulants (e.g., heparin or dicumarol derivatives) have an increased risk of bleeding complications if given ketorolac tromethamine concurrently; therefore, physicians should administer such concomitant therapy only extremely cautiously. The concurrent use of ketorolac tromethamine and therapy that affects hemostasis, including prophylactic low-dose heparin (2500 to 5000 units q12h), warfarin and dextrans have not been studied extensively, but may also be associated with an increased risk of bleeding. Until data from such studies are available, physicians should carefully weigh the benefits against the risks and use such concomitant therapy in these patients only extremely cautiously. Patients receiving therapy that affects hemostasis should be monitored closely.

In postmarketing experience, postoperative hematomas and other signs of wound bleeding have been reported in association with the peri-operative use of IV or IM dosing of ketorolac tromethamine. Therefore, peri-operative use of ketorolac tromethamine should be avoided and postoperative use be undertaken with caution when hemostasis is critical (see PRECAUTIONS).

Renal Effects

Long-term administration of NSAIDs has resulted in renal papillary necrosis and other renal injury. Renal toxicity has also been seen in patients in whom renal prostaglandins have a compensatory role in the maintenance of renal perfusion. In these patients, administration of a NSAID may cause a dose- dependent reduction in prostaglandin formation and, secondarily, in renal blood flow, which may precipitate overt renal decompensation. Patients at greatest risk of this reaction are those with impaired renal function, heart failure, liver dysfunction, those taking diuretics and ACE inhibitors, and the elderly. Discontinuation of NSAID therapy is usually followed by recovery to the pretreatment state.

Ketorolac tromethamine and its metabolites are eliminated primarily by the kidneys, which, in patients with reduced creatinine clearance, will result in diminished clearance of the drug (see CLINICAL PHARMACOLOGY). Therefore, ketorolac tromethamine should be used with caution in patients with impaired renal function (see DOSAGE AND ADMINISTRATION) and such patients should be followed closely. With the use of ketorolac tromethamine, there have been reports of acute renal failure, interstitial nephritis and nephrotic syndrome.

Impaired Renal Function

Ketorolac tromethamine is contraindicated in patients with serum creatinine concentrations indicating advanced renal impairment (see CONTRAINDICATIONS). Ketorolac tromethamine should be used with caution in patients with impaired renal function or a history of kidney disease because it is a potent inhibitor of prostaglandin synthesis. Because patients with underlying renal insufficiency are at increased risk of developing acute renal decompensation or failure, the risks and benefits should be assessed prior to giving ketorolac tromethamine to these patients.

Anaphylactoid Reactions

As with other NSAIDs, anaphylactoid reactions may occur in patients without a known previous exposure or hypersensitivity to ketorolac tromethamine. Ketorolac tromethamine should not be given to patients with the aspirin triad. This symptom complex typically occurs in asthmatic patients who experience rhinitis with or without nasal polyps, or who exhibit severe, potentially fatal bronchospasm after taking aspirin or other NSAIDs (see CONTRAINDICATIONS and PRECAUTIONS, Preexisting Asthma). Anaphylactoid reactions, like anaphylaxis, may have a fatal outcome. Emergency help should be sought in cases where an anaphylactoid reaction occurs.

Cardiovascular Effects

Cardiovascular Thrombotic Events

Clinical trials of several COX-2 selective and nonselective NSAIDs of up to three years duration have shown an increased risk of serious cardiovascular (CV) thrombotic events, including myocardial infarction (MI) and stroke, which can be fatal. Based on available data, it is unclear that the risk for CV thrombotic events is similar for all NSAIDs. The relative increase in serious CV thrombotic events over baseline conferred by NSAID use appears to be similar in those with and without known CV disease or risk factors for CV disease. However, patients with known CV disease or risk factors had a higher absolute incidence of excess serious CV thrombotic events, due to their increased baseline rate. Some observational studies found that this increased risk of serious CV thrombotic events began as early as the first weeks of treatment. The increase in CV thrombotic risk has been observed most consistently at higher doses.

To minimize the potential risk for an adverse CV event in NSAID-treated patients, use the lowest effective dose for the shortest duration possible. Physicians and patients should remain alert for the development of such events, throughout the entire treatment course, even in the absence of previous CV symptoms. Patients should be informed about the symptoms of serious CV events and the steps to take if they occur.

There is no consistent evidence that concurrent use of aspirin mitigates the increased risk of serious CV thrombotic events associated with NSAID use. The concurrent use of aspirin and an NSAID, such as ketorolac tromethamine, increases the risk of serious gastrointestinal (GI) events (see WARNINGS).

Status Post Coronary Artery Bypass Graft (CABG) Surgery

Two large, controlled clinical trials of a COX-2 selective NSAID for the treatment of pain in the first 10 to 14 days following CABG surgery found an increased incidence of myocardial infarction and stroke. NSAIDs are contraindicated in the setting of CABG (see CONTRAINDICATIONS).

Post-MI Patients

Observational studies conducted in the Danish National Registry have demonstrated that patients treated with NSAIDs in the post-MI period were at increased risk of reinfarction, CV-related death, and all- cause mortality beginning in the first week of treatment. In this same cohort, the incidence of death in the first-year post MI was 20 per 100 person years in NSAID-treated patients compared to 12 per 100 person years in non-NSAID exposed patients. Although the absolute rate of death declined somewhat after the first-year post-MI, the increased relative risk of death in NSAID users persisted over at least the next four years of follow-up.

Avoid the use of ketorolac tromethamine tablets in patients with a recent MI unless the benefits are expected to outweigh the risk of recurrent CV thrombotic events. If ketorolac tromethamine tablets are used in patients with a recent MI, monitor patients for signs of cardiac ischemia.

Hypertension

NSAIDs, including ketorolac tromethamine, can lead to onset of new hypertension or worsening of preexisting hypertension, either of which may contribute to the increased incidence of CV events. Patients taking thiazides or loop diuretics may have impaired response to these therapies when taking NSAIDs. NSAIDs, including ketorolac tromethamine, should be used with caution in patients with hypertension. Blood pressure (BP) should be monitored closely during the initiation of NSAID treatment and throughout the course of therapy.

Heart Failure and Edema

The Coxib and traditional NSAID Trialists' Collaboration meta-analysis of randomized controlled trials demonstrated an approximately two-fold increase in hospitalizations for heart failure in COX-2 selective-treated patients and nonselective NSAID-treated patients compared to placebo-treated patients. In a Danish National Registry study of patients with heart failure, NSAID use increased the risk of MI, hospitalization for heart failure, and death.

Additionally, fluid retention and edema have been observed in some patients treated with NSAIDs. Use of ketorolac tromethamine may blunt the CV effects of several therapeutic agents used to treat these medical conditions [e.g., diuretics, ACE inhibitors, or angiotensin receptor blockers (ARBs)] (see DRUG INTERACTIONS).

Avoid the use of ketorolac tromethamine tablets in patients with severe heart failure unless the benefits are expected to outweigh the risk of worsening heart failure. If ketorolac tromethamine tablets are used in patients with severe heart failure, monitor patients for signs of worsening heart failure.

Serious Skin Reactions

NSAIDs, including ketorolac tromethamine, can cause serious skin adverse reactions such as exfoliative dermatitis, Stevens-Johnson Syndrome (SJS), and toxic epidermal necrolysis (TEN), which can be fatal. NSAIDs can also cause fixed drug eruption (FDE). FDE may present as a more severe variant known as generalized bullous fixed drug eruption (GBFDE), which can be life-threatening. These serious events may occur without warning. Inform patients about the signs and symptoms of serious skin reactions, and to discontinue the use of ketorolac tromethamine tablets at the first appearance of skin rash or any other sign of hypersensitivity. Ketorolac tromethamine tablets is contraindicated in patients with previous serious skin reactions to NSAIDs (see CONTRAINDICATIONS).

Drug Reaction with Eosinophilia and Systemic Symptoms (DRESS)

Drug Reaction with Eosinophilia and Systemic Symptoms (DRESS) has been reported in patients taking NSAIDs such as ketorolac tromethamine tablets. Some of these events have been fatal or life- threatening. DRESS typically, although not exclusively, presents with fever, rash, lymphadenopathy, and/or facial swelling. Other clinical manifestations may include hepatitis, nephritis, hematological abnormalities, myocarditis, or myositis. Sometimes symptoms of DRESS may resemble an acute viral infection. Eosinophilia is often present. Because this disorder is variable in its presentation, other organ systems not noted here may be involved. It is important to note that early manifestations of hypersensitivity, such as fever or lymphadenopathy, may be present even though rash is not evident. If such signs or symptoms are present, discontinue ketorolac tromethamine tablets and evaluate the patient immediately.

Fetal Toxicity

Premature Closure of Fetal Ductus Arteriosus:

Avoid use of NSAIDs, including ketorolac tromethamine tablets, in pregnant women at about 30 weeks gestation and later. NSAIDs including ketorolac tromethamine tablets, increase the risk of premature closure of the fetal ductus arteriosus at approximately this gestational age.

Oligohydramnios/Neonatal Renal Impairment:

Use of NSAIDs, including ketorolac tromethamine tablets, at about 20 weeks gestation or later in pregnancy may cause fetal renal dysfunction leading to oligohydramnios and, in some cases, neonatal renal impairment. These adverse outcomes are seen, on average, after days to weeks of treatment, although oligohydramnios has been infrequently reported as soon as 48 hours after NSAID initiation. Oligohydramnios is often, but not always, reversible with treatment discontinuation. Complications of prolonged oligohydramnios may, for example, include limb contractures and delayed lung maturation. In some postmarketing cases of impaired neonatal renal function, invasive procedures such as exchange transfusion or dialysis were required.

If NSAID treatment is necessary between about 20 weeks and 30 weeks gestation, limit ketorolac tromethamine tablets use to the lowest effective dose and shortest duration possible. Consider ultrasound monitoring of amniotic fluid if ketorolac tromethamine tablets treatment extends beyond 48 hours. Discontinue ketorolac tromethamine tablets if oligohydramnios occurs and follow up according to clinical practice (see PRECAUTIONS; Pregnancy).

PRECAUTIONS

General

Ketorolac tromethamine cannot be expected to substitute for corticosteroids or to treat corticosteroid insufficiency. Abrupt discontinuation of corticosteroids may lead to disease exacerbation. Patients on prolonged corticosteroid therapy should have their therapy tapered slowly if a decision is made to discontinue corticosteroids.

The pharmacological activity of ketorolac tromethamine in reducing inflammation may diminish the utility of this diagnostic sign in detecting complications of presumed noninfectious, painful conditions.

Hepatic Effect

Ketorolac tromethamine should be used with caution in patients with impaired hepatic function or a history of liver disease. Borderline elevations of one or more liver tests may occur in up to 15% of patients taking NSAIDs including ketorolac tromethamine. These laboratory abnormalities may progress, may remain unchanged, or may be transient with continuing therapy. Notable elevations of ALT or AST (approximately three or more times the upper limit of normal) have been reported in approximately 1% of patients in clinical trials with NSAIDs. In addition, rare cases of severe hepatic reactions, including jaundice and fatal fulminant hepatitis, liver necrosis and hepatic failure, some of them with fatal outcomes have been reported.

A patient with symptoms and/or signs suggesting liver dysfunction, or in whom an abnormal liver test has occurred, should be evaluated for evidence of the development of a more severe hepatic reaction while on therapy with ketorolac tromethamine. If clinical signs and symptoms consistent with liver disease develop, or if systemic manifestations occur (e.g., eosinophilia, rash, etc.), ketorolac tromethamine should be discontinued.

Hematologic Effect

Anemia is sometimes seen in patients receiving NSAIDs, including ketorolac tromethamine. This may be due to fluid retention, occult or gross GI blood loss, or an incompletely described effect upon erythropoiesis. Patients on long-term treatment with NSAIDs, including ketorolac tromethamine, should have their hemoglobin or hematocrit checked if they exhibit any signs or symptoms of anemia. NSAIDs inhibit platelet aggregation and have been shown to prolong bleeding time in some patients. Unlike aspirin, their effect on platelet function is quantitatively less, of shorter duration, and reversible.

Patients receiving ketorolac tromethamine who may be adversely affected by alterations in platelet function, such as those with coagulation disorders or patients receiving anticoagulants, should be carefully monitored.

Preexisting Asthma

Patients with asthma may have aspirin-sensitive asthma. The use of aspirin in patients with aspirin- sensitive asthma has been associated with severe bronchospasm which can be fatal. Since cross reactivity, including bronchospasm, between aspirin and other nonsteroidal anti-inflammatory drugs has been reported in such aspirin-sensitive patients, ketorolac tromethamine should not be administered to patients with this form of aspirin sensitivity and should be used with caution in patients with preexisting asthma.

Information for Patients

Ketorolac tromethamine is a potent NSAID and may cause serious side effects such as gastrointestinal bleeding or kidney failure, which may result in hospitalization and even fatal outcome.

Physicians, when prescribing ketorolac tromethamine, should inform their patients or their guardians of the potential risks of ketorolac tromethamine treatment (see Boxed WARNING, WARNINGS, PRECAUTIONS, and ADVERSE REACTIONS sections), instruct patients to seek medical advice if they develop treatment-related adverse events, and advise patients not to give ketorolac tromethamine tablets to other family members and to discard any unused drug.

Remember that the total combined duration of use of ketorolac tromethamine tablets and IV or IM dosing of ketorolac tromethamine is not to exceed 5 days in adults. Ketorolac tromethamine tablets are not indicated for use in pediatric patients.

Patients should be informed of the following information before initiating therapy with an NSAID and periodically during the course of ongoing therapy. Patients should also be encouraged to read the NSAID Medication Guide that accompanies each prescription dispensed.

1. Cardiovascular Thrombotic Events Advise patients to be alert for the symptoms of cardiovascular thrombotic events, including chest pain, shortness of breath, weakness, or slurring of speech, and to report any of these symptoms to their health care provider immediately (see WARNINGS).
2. Ketorolac tromethamine, like other NSAIDs, can cause GI discomfort and rarely, serious GI side effects, such as ulcers and bleeding, which may result in hospitalization and even death. Although serious GI tract ulcerations and bleeding can occur without warning symptoms, patients should be alert for the signs and symptoms of ulcerations and bleeding, and should ask for medical advice when observing any indicative sign or symptoms including epigastric pain, dyspepsia, melena, and hematemesis. Patients should be apprised of the importance of this follow-up (see WARNINGS, Gastrointestinal Effects – Risk of Ulceration, Bleeding, and Perforation).
3. Serious Skin Reactions, including DRESS Advise patients to stop taking ketorolac tromethamine tablets immediately if they develop any type of rash or fever and to contact their healthcare provider as soon as possible (see WARNINGS).
4. Heart Failure and Edema Advise patients to be alert for the symptoms of congestive heart failure including shortness of breath, unexplained weight gain, or edema and to contact their healthcare provider if such symptoms occur (see WARNINGS).
5. Patients should promptly report signs or symptoms of unexplained weight gain or edema to their physicians.
6. Patients should be informed of the warning signs and symptoms of hepatotoxicity (e.g., nausea, fatigue, lethargy, pruritus, jaundice, right upper quadrant tenderness, and "flu-like" symptoms). If these occur, patients should be instructed to stop therapy and seek immediate medical therapy.
7. Patients should be informed of the signs of an anaphylactoid reaction (e.g., difficulty breathing, swelling of the face or throat). If these occur, patients should be instructed to seek immediate emergency help (see WARNINGS).
8. Fetal Toxicity Inform pregnant women to avoid use of ketorolac tromethamine tablets and other NSAIDs starting at 30 weeks gestation because of the risk of the premature closing of the fetal ductus arteriosus. If treatment with ketorolac tromethamine tablets is needed for a pregnant woman between about 20 to 30 weeks gestation, advise her that she may need to be monitored for oligohydramnios, if treatment continues for longer than 48 hours (see WARNINGS; Fetal Toxicity, PRECAUTIONS; Pregnancy).

Laboratory Tests

Because serious GI tract ulcerations and bleeding can occur without warning symptoms, physicians should monitor for signs or symptoms of GI bleeding. Patients on long-term treatment with NSAIDs, should have their CBC and a chemistry profile checked periodically. If clinical signs and symptoms consistent with liver or renal disease develop, systemic manifestations occur (e.g., eosinophilia, rash, etc.) or if abnormal liver tests persist or worsen, ketorolac tromethamine should be discontinued.

Drug Interactions

Ketorolac is highly bound to human plasma protein (mean 99.2%). There is no evidence in animal or human studies that ketorolac tromethamine induces or inhibits hepatic enzymes capable of metabolizing itself or other drugs.

Warfarin, Digoxin, Salicylate, and Heparin

The in vitro binding of warfarin to plasma proteins is only slightly reduced by ketorolac tromethamine (99.5% control vs 99.3%) when ketorolac plasma concentrations reach 5 to 10 mcg/mL. Ketorolac does not alter digoxin protein binding. In vitro studies indicate that, at therapeutic concentrations of salicylate (300 mcg/mL), the binding of ketorolac was reduced from approximately 99.2% to 97.5%, representing a potential twofold increase in unbound ketorolac plasma levels. Therapeutic concentrations of digoxin, warfarin, ibuprofen, naproxen, piroxicam, acetaminophen, phenytoin and tolbutamide did not alter ketorolac tromethamine protein binding.

In a study involving 12 adult volunteers, ketorolac tromethamine tablets were coadministered with a single dose of 25 mg warfarin, causing no significant changes in pharmacokinetics or pharmacodynamics of warfarin. In another study, ketorolac tromethamine dosed IV or IM was given with two doses of 5000 U of heparin to 11 healthy volunteers, resulting in a mean template bleeding time of 6.4 minutes (3.2 to 11.4 min) compared to a mean of 6 minutes (3.4 to 7.5 min) for heparin alone and 5.1 minutes (3.5 to 8.5 min) for placebo. Although these results do not indicate a significant interaction between ketorolac tromethamine and warfarin or heparin, the administration of ketorolac tromethamine to patients taking anticoagulants should be done extremely cautiously, and patients should be closely monitored (see WARNINGS and PRECAUTIONS, Hematologic Effect).

The effects of warfarin and NSAIDs, in general, on GI bleeding are synergistic, such that the users of both drugs together have a risk of serious GI bleeding higher than the users of either drug alone.

Aspirin

When ketorolac tromethamine is administered with aspirin, its protein binding is reduced, although the clearance of free ketorolac tromethamine is not altered. The clinical significance of this interaction is not known; however, as with other NSAIDs, concomitant administration of ketorolac tromethamine and aspirin is not generally recommended because of the potential of increased adverse effects.

Diuretics

Clinical studies, as well as postmarketing observations, have shown that ketorolac tromethamine can reduce the natriuretic effect of furosemide and thiazides in some patients. This response has been attributed to inhibition of renal prostaglandin synthesis. During concomitant therapy with NSAIDs, the patient should be observed closely for signs of renal failure (see WARNINGS, Renal Effects), as well as to assure diuretic efficacy.

Probenecid

Concomitant administration of ketorolac tromethamine tablets and probenecid resulted in decreased clearance and volume of distribution of ketorolac and significant increases in ketorolac plasma levels (total AUC increased approximately threefold from 5.4 to 17.8 mcg/h/mL) and terminal half-life increased approximately twofold from 6.6 to 15.1 hours. Therefore, concomitant use of ketorolac tromethamine and probenecid is contraindicated.

Lithium

NSAIDs have produced an elevation of plasma lithium levels and a reduction in renal lithium clearance. The mean minimum lithium concentration increased 15% and the renal clearance was decreased by approximately 20%. These effects have been attributed to inhibition of renal prostaglandin synthesis by the NSAID. Thus, when NSAIDs and lithium are administered concurrently, subjects should be observed carefully for signs of lithium toxicity.

Methotrexate

NSAIDs have been reported to competitively inhibit methotrexate accumulation in rabbit kidney slices. This may indicate that they could enhance the toxicity of methotrexate. Caution should be used when NSAIDs are administered concomitantly with methotrexate.

ACE Inhibitors/Angiotensin II Receptor Antagonists

Concomitant use of ACE inhibitors and/or angiotensin II receptor antagonists may increase the risk of renal impairment, particularly in volume-depleted patients.

Reports suggest that NSAIDs may diminish the antihypertensive effect of ACE inhibitors and/or angiotensin II receptor antagonists. This interaction should be given consideration in patients taking NSAIDs concomitantly with ACE inhibitors and/or angiotensin II receptor antagonists.

Antiepileptic Drugs

Sporadic cases of seizures have been reported during concomitant use of ketorolac tromethamine and antiepileptic drugs (phenytoin, carbamazepine).

Psychoactive Drugs

Hallucinations have been reported when ketorolac tromethamine was used in patients taking psychoactive drugs (fluoxetine, thiothixene, alprazolam).

Pentoxifylline

When ketorolac tromethamine is administered concurrently with pentoxifylline, there is an increased tendency to bleeding.

Nondepolarizing Muscle Relaxants

In postmarketing experience there have been reports of a possible interaction between ketorolac tromethamineIV/IMand nondepolarizing muscle relaxants that resulted in apnea. The concurrent use of ketorolac tromethamine with muscle relaxants has not been formally studied.

Selective Serotonin Reuptake Inhibitors (SSRIs)

There is an increased risk of gastrointestinal bleeding when selective serotonin reuptake inhibitors (SSRIs) are combined with NSAIDs. Caution should be used when NSAIDs are administered concomitantly with SSRIs.

Carcinogenesis, Mutagenesis, Impairment of Fertility

An 18 month study in mice with oral doses of ketorolac tromethamine at 2 mg/kg/day (0.9 times the human systemic exposure at the recommended IM or IV dose of 30 mg qid, based on area-under-the- plasma-concentration curve [AUC]), and a 24 month study in rats at 5 mg/kg/day (0.5 times the human AUC) showed no evidence of tumorigenicity.

Ketorolac tromethamine was not mutagenic in the Ames test, unscheduled DNA synthesis and repair, and in forward mutation assays. Ketorolac tromethamine did not cause chromosome breakage in the in vivo mouse micronucleus assay. At 1590 mcg/mL and at higher concentrations, ketorolac tromethamine increased the incidence of chromosomal aberrations in Chinese hamster ovarian cells.

Impairment of fertility did not occur in male or female rats at oral doses of 9 mg/kg (0.9 times the human AUC) and 16 mg/kg (1.6 times the human AUC) of ketorolac tromethamine, respectively.

Pregnancy

Risk Summary

Use of NSAIDs, including ketorolac tromethamine tablets, can cause premature closure of the fetal ductus arteriosus and fetal renal dysfunction leading to oligohydramnios and, in some cases, neonatal renal impairment. Because of these risks, limit dose and duration of ketorolac tromethamine tablets use between about 20 and 30 weeks of gestation, and avoid ketorolac tromethamine tablets use at about 30 weeks of gestation and later in pregnancy (see WARNINGS; Fetal Toxicity).

Premature Closure of Fetal Ductus Arteriosus

Use of NSAIDs, including ketorolac tromethamine tablets, at about 30 weeks gestation or later in pregnancy increases the risk of premature closure of the fetal ductus arteriosus.

Oligohydramnios/Neonatal Renal Impairment

Use of NSAIDs at about 20 weeks gestation or later in pregnancy has been associated with cases of fetal renal dysfunction leading to oligohydramnios, and in some cases, neonatal renal impairment.

Data from observational studies regarding other potential embryofetal risks of NSAID use in women in the first or second trimesters of pregnancy are inconclusive. Animal reproduction studies have been performed during organogenesis using daily oral doses of ketorolac tromethamine at 3.6 mg/kg (0.37 times the human AUC) in rabbits and at 10 mg/kg (1 times the human AUC) in rats. Results of these studies did not reveal evidence of teratogenicity to the fetus. However, animal reproduction studies are not always predictive of human response. Based on animal data, prostaglandins have been shown to have an important role in endometrial vascular permeability, blastocyst implantation, and decidualization. In animal studies, administration of prostaglandin synthesis inhibitors such as ketorolac tromethamine, resulted in increased pre- and post-implantation loss. Prostaglandins also have been shown to have an important role in fetal kidney development. In published animal studies, prostaglandin synthesis inhibitors have been reported to impair kidney development when administered at clinically relevant doses. The estimated background risk of major birth defects and miscarriage for the indicated population(s) is unknown. All pregnancies have a background risk of birth defect, loss, or other adverse outcomes. In the U.S. general population the estimated background risk of major birth defects and miscarriage in clinically recognized pregnancies is 2 to 4% and 15 to 20% respectively.

Clinical Considerations

Fetal/Neonatal Adverse Reactions

Premature Closure of Fetal Ductus Arteriosus:

Avoid use of NSAIDs in women at about 30 weeks gestation and later in pregnancy, because NSAIDs, including ketorolac tromethamine tablets, can cause premature closure of the fetal ductus arteriosus (see WARNINGS; Fetal Toxicity).

Oligohydramnios/Neonatal Renal Impairment

If an NSAID is necessary at about 20 weeks gestation or later in pregnancy, limit the use to the lowest effective dose and shortest duration possible. If ketorolac tromethamine tablets treatment extends beyond 48 hours, consider monitoring with ultrasound for oligohydramnios. If oligohydramnios occurs, discontinue ketorolac tromethamine tablets and follow up according to clinical practice (see WARNINGS; Fetal Toxicity).

Data

Human Data

Premature Closure of Fetal Ductus Arteriosus:

Published literature reports that the use of NSAIDs at about 30 weeks of gestation and later in pregnancy may cause premature closure of the fetal ductus arteriosus.

Oligohydramnios/Neonatal Renal Impairment:

Published studies and postmarketing reports describe maternal NSAID use at about 20 weeks gestation or later in pregnancy associated with fetal renal dysfunction leading to oligohydramnios, and in some cases, neonatal renal impairment. These adverse outcomes are seen, on average, after days to weeks of treatment, although oligohydramnios has been infrequently reported as soon as 48 hours after NSAID initiation. In many cases, but not all, the decrease in amniotic fluid was transient and reversible with cessation of the drug. There have been a limited number of case reports of maternal NSAID use and neonatal renal dysfunction without oligohydramnios, some of which were irreversible. Some cases of neonatal renal dysfunction required treatment with invasive procedures, such as exchange transfusion or dialysis.

Methodological limitations of these postmarketing studies and reports include lack of a control group; limited information regarding dose, duration, and timing of drug exposure; and concomitant use of other medications. These limitations preclude establishing a reliable estimate of the risk of adverse fetal and neonatal outcomes with maternal NSAID use. Because the published safety data on neonatal outcomes involved mostly preterm infants, the generalizability of certain reported risks to the full-term infant exposed to NSAIDs through maternal use is uncertain.

Animal Data

Because of the known effects of nonsteroidal anti-inflammatory drugs on the fetal cardiovascular system (closure of ductus arteriosus), use during pregnancy (particularly late pregnancy) should be avoided. Oral doses of ketorolac tromethamine at 1.5 mg/kg (0.14 times the human AUC), administered after gestation Day 17, caused dystocia and higher pup mortality in rats.

Labor and Delivery

The use of ketorolac tromethamine is contraindicated in labor and delivery because, through its prostaglandin synthesis inhibitory effect, it may adversely affect fetal circulation and inhibit uterine contractions, thus increasing the risk of uterine hemorrhage (see CONTRAINDICATIONS).

Effects on Fertility

The use of ketorolac tromethamine, as with any drug known to inhibit cyclooxygenase/prostaglandin synthesis, may impair fertility and is not recommended in women attempting to conceive. In women who have difficulty conceiving or are undergoing investigation of infertility, withdrawal of ketorolac tromethamine should be considered.

Nursing Mothers

Limited data from one published study involving 10 breastfeeding women 2 to 6 days postpartum showed low levels of ketorolac in breast milk. Levels were undetectable (less than 5 ng/mL) in 4 of the patients. After a single administration of 10 mg of ketorolac tromethamine tablets, the maximum milk concentration observed was 7.3 ng/mL, and the maximum milk-to-plasma ratio was 0.037. After 1 day of dosing (10 mg every 6 hours), the maximum milk concentration was 7.9 ng/mL, and the maximum milk-to- plasma ratio was 0.025. Assuming a daily intake of 400 to 1,000 mL of human milk per day and a maternal body weight of 60 kg, the calculated maximum daily infant exposure was 0.00263 mg/kg/day, which is 0.4% of the maternal weight-adjusted dose.

Exercise caution when ketorolac is administered to a nursing woman. Available information has not shown any specific adverse events in nursing infants; however, instruct patients to contact their infant's health care provider if they note any adverse events.

Pediatric Use

Ketorolac tromethamine tablets are not indicated for use in pediatric patients. The safety and effectiveness of ketorolac tromethamine tablets in pediatric patients below the age of 17 have not been established.

Geriatric Use (≥ 65 Years of Age)

Because ketorolac tromethamine may be cleared more slowly by the elderly (see CLINICAL PHARMACOLOGY) who are also more sensitive to the dose-related adverse effects of NSAIDs (see WARNINGS, Gastrointestinal Effects – Risk of Ulceration, Bleeding, and Perforation), extreme caution, reduced dosages (see DOSAGE AND ADMINISTRATION), and careful clinical monitoring must be used when treating the elderly with ketorolac tromethamine.

ADVERSE REACTIONS

Adverse reaction rates increase with higher doses of ketorolac tromethamine. Practitioners should be alert for the severe complications of treatment with ketorolac tromethamine, such as GI ulceration, bleeding and perforation, postoperative bleeding, acute renal failure, anaphylactic and anaphylactoid reactions and liver failure (see Boxed WARNING, WARNINGS, PRECAUTIONS, and DOSAGE AND ADMINISTRATION). These NSAID-related complications can be serious in certain patients for whom ketorolac tromethamine is indicated, especially when the drug is used inappropriately.

In patients taking ketorolac tromethamine or other NSAIDs in clinical trials, the most frequently reported adverse experiences in approximately 1% to 10% of patients are:

Gastrointestinal (GI) experiences including:
Abdominal Pain [Incidence greater than 10%] | Constipation/Diarrhea | Dyspepsia
Flatulence | GI Fullness | GI Ulcers (gastric/duodenal)
Gross Bleeding/Perforation | Heartburn | Nausea
Stomatitis | Vomiting
Other experiences:
Abnormal Renal Function | Anemia | Dizziness
Drowsiness | Edema | Elevated Liver Enzymes
Headaches | Hypertension | Increased Bleeding Time
Injection Site Pain | Pruritus | Purpura
Rashes | Tinnitus | Sweating

Additional adverse experiences reported occasionally (< 1% in patients taking ketorolac tromethamine or other NSAIDs in clinical trials) include:

Body as a Whole: fever, infections, sepsis

Cardiovascular: congestive heart failure, palpitation, pallor, tachycardia, syncope

Dermatologic: alopecia, photosensitivity, urticaria

Gastrointestinal: anorexia, dry mouth, eructation, esophagitis, excessive thirst, gastritis, glossitis, hematemesis, hepatitis, increased appetite, jaundice, melena, rectal bleeding

Hemic and Lymphatic: ecchymosis, eosinophilia, epistaxis, leukopenia, thrombocytopenia

Metabolic and Nutritional: weight change

Nervous System: abnormal dreams, abnormal thinking, anxiety, asthenia, confusion, depression, euphoria, extrapyramidal symptoms, hallucinations, hyperkinesis, inability to concentrate, insomnia, nervousness, paresthesia, somnolence, stupor, tremors, vertigo, malaise

Reproductive, female: infertility

Respiratory: asthma, cough, dyspnea, pulmonary edema, rhinitis

Special Senses: abnormal taste, abnormal vision, blurred vision, hearing loss

Urogenital: cystitis, dysuria, hematuria, increased urinary frequency, interstitial nephritis, oliguria/polyuria, proteinuria, renal failure, urinary retention

Other rarely observed reactions (reported from postmarketing experience in patients taking ketorolac tromethamine or other NSAIDs) are:

Body as a Whole: angioedema, death, hypersensitivity reactions such as anaphylaxis, anaphylactoid reaction, laryngeal edema, tongue edema (see WARNINGS), myalgia

Cardiovascular: arrhythmia, bradycardia, chest pain, flushing, hypotension, myocardial infarction, vasculitis

Dermatologic: exfoliative dermatitis, erythema multiforme, Lyell's syndrome, bullous reactions including Stevens-Johnson syndrome and toxic epidermal necrolysis, and fixed drug eruption (FDE)

Gastrointestinal: acute pancreatitis, liver failure, ulcerative stomatitis, exacerbation of inflammatory bowel disease (ulcerative colitis, Crohn's disease)

Hemic and Lymphatic: agranulocytosis, aplastic anemia, hemolytic anemia, lymphadenopathy, pancytopenia, postoperative wound hemorrhage (rarely requiring blood transfusion - see Boxed WARNING, WARNINGS, and PRECAUTIONS)

Metabolic and Nutritional: hyperglycemia, hyperkalemia, hyponatremia Nervous System: aseptic meningitis, convulsions, coma, psychosis Respiratory: bronchospasm, respiratory depression, pneumonia

Special Senses: conjunctivitis

Urogenital: flank pain with or without hematuria and/or azotemia, hemolytic uremic syndrome

Postmarketing Surveillance Study

A large postmarketing observational, nonrandomized study, involving approximately 10,000 patients receiving ketorolac tromethamineIV/IM, demonstrated that the risk of clinically serious gastrointestinal (GI) bleeding was dose-dependent (see Tables 3A and 3B). This was particularly true in elderly patients who received an average daily dose greater than 60 mg/day of ketorolac tromethamineIV/IM (see Table 3A).

Table 3: Incidence of Clinically Serious GI Bleeding as Related to Age, Total Daily Dose, and History of GI Perforation, Ulcer, Bleeding (PUB) After up to 5 Days of Treatment With Ketorolac Tromethamine IV/IM

A. Adult Patients Without History of PUB
Age of Patients | Total Daily Dose of Ketorolac Tromethamine IV/IM
Age of Patients | ≤ 60 mg | > 60 to 90 mg | > 90 to 120 mg | > 120 mg
< 65 years of age | 0.4% | 0.4% | 0.9% | 4.6%
≥ 65 years of age | 1.2% | 2.8% | 2.2% | 7.7%
B. Adult Patients With History of PUB
Age of Patients | Total Daily Dose of Ketorolac Tromethamine IV/IM
Age of Patients | ≤ 60 mg | > 60 to 90 mg | > 90 to 120 mg | > 120 mg
< 65 years of age | 2.1% | 4.6% | 7.8% | 15.4%
≥ 65 years of age | 4.7% | 3.7% | 2.8% | 25%

OVERDOSAGE

Symptoms and Signs

Symptoms following acute NSAID overdoses are usually limited to lethargy, drowsiness, nausea, vomiting, and epigastric pain, which are generally reversible with supportive care. Gastrointestinal bleeding can occur. Hypertension, acute renal failure, respiratory depression and coma may occur, but are rare. Anaphylactoid reactions have been reported with therapeutic ingestion of NSAIDs, and may occur following an overdose.

Treatment

Patients should be managed by symptomatic and supportive care following a NSAIDs overdose. There are no specific antidotes. Emesis and/or activated charcoal (60 g to 100 g in adults, 1 g/kg to 2 g/kg in children) and/or osmotic cathartic may be indicated in patients seen within 4 hours of ingestion with symptoms or following a large oral overdose (5 to 10 times the usual dose). Forced diuresis, alkalization of urine, hemodialysis or hemoperfusion may not be useful due to high protein binding.

Single overdoses of ketorolac tromethamine have been variously associated with abdominal pain, nausea, vomiting, hyperventilation, peptic ulcers and/or erosive gastritis and renal dysfunction which have resolved after discontinuation of dosing.

DOSAGE AND ADMINISTRATION

Carefully consider the potential benefits and risks of ketorolac tromethamine tablets and other treatment options before deciding to use ketorolac tromethamine tablets. Use the lowest effective dose for the shortest duration consistent with individual patient treatment goals. In adults, the combined duration of use of IV or IM dosing of ketorolac tromethamine and ketorolac tromethamine tablets is not to exceed 5 days. In adults, the use of ketorolac tromethamine tablets is only indicated as continuation therapy to IV or IM dosing of ketorolac tromethamine.

Transition from IV or IM dosing of ketorolac tromethamine (single- or multiple-dose) to multiple-dose ketorolac tromethamine tablets:

Patients age 17 to 64: 20 mg PO once followed by 10 mg q4 to 6 hours prn not > 40 mg/day

Patients age ≥ 65, renally impaired, and/or weight < 50 kg (110 lbs): 10 mg PO once followed by 10 mg q4 to 6 hours prn not > 40 mg/day

Note:

Oral formulation should not be given as an initial dose. Use minimum effective dose for the individual patient.

Do not shorten dosing interval of 4 to 6 hours.

Total duration of treatment in adult patients: the combined duration of use of IV or IM dosing of ketorolac tromethamine and ketorolac tromethamine tablets is not to exceed 5 days.

The following table summarizes ketorolac tromethamine tablet dosing instructions in terms of age group:

Table 4: Summary of Dosing Instructions

Patient Population | Ketorolac Tromethamine Tablets (following IV or IM dosing of ketorolac tromethamine)
Age < 17 years | Oral not approved
Adult Age 17 to 64 years | 20 mg once, then 10 mg q4 to 6 hours prn not > 40 mg/day
Adult Age ≥ 65 years, renally impaired, and/or weight < 50 kg | 10 mg once, then 10 mg q4 to 6 hours prn not > 40 mg/day

HOW SUPPLIED

Ketorolac Tromethamine Tablets USP are available as follows:

10 mg: White, round, bi-convex, unscored film-coated tablets, debossed "A" on one side and "39" on other side. They are available

Cartons of 30 film-coated tablets (10 film-coated tablets each blister pack x 3), NDC 0904-7303-04

WARNING: This Unit Dose package is not child resistant and is Intended for Institutional Use Only. Keep this and all drugs out of the reach of children.

Store at 20° to 25°C (68° to 77°F) [See USP Controlled Room Temperature].

Dispense in a tight, light-resistant container as defined in the USP, with a child-resistant closure (as required).

PROTECT FROM LIGHT AND EXCESSIVE HUMIDITY.

Manufactured by:

Aavis Pharmaceuticals

Hoschton, GA 30548

Code. L7048/01

Rev. 08/2024

Distributed by:

Dr Reddy's Laboratories Inc.

Princeton, NJ 08540 USA

Packaged and Distributed by:

MAJOR® PHARMACEUTICALS

Indianapolis, IN 46268 USA

Refer to package label for Distributor's NDC Number

MEDICATION GUIDE

MEDICATION GUIDE FOR NONSTEROIDAL ANTI-INFLAMMATORY DRUGS (NSAIDS)

What is the most important information I should know about medicines called Nonsteroidal Anti-inflammatory Drugs (NSAIDs)?

NSAIDs can cause serious side effects, including:

◾ Increased risk of a heart attack or stroke that can lead to death . This risk may happen early in treatment and may increase:
◽ with increasing doses of NSAIDs
◽ with longer use of NSAIDs

Do not take NSAIDs right before or after a heart surgery called a "coronary artery bypass graft (CABG)."

Avoid taking NSAIDs after a recent heart attack, unless your healthcare provider tells you to. You may have an increased risk of another heart attack if you take NSAIDs after a recent heart attack.

◾ Increased risk of bleeding, ulcers, and tears (perforation) of the esophagus (tube leading from the mouth to the stomach), stomach and intestines:
◽ anytime during use
◽without warning symptoms
◽that may cause death

The risk of getting an ulcer or bleeding increases with:

◾ past history of stomach ulcers, or stomach or intestinal bleeding with use of NSAIDs
◾ taking medicines called "corticosteroids", "anticoagulants", "SSRIs", or "SNRIs"

◽increasing doses of NSAIDs
◽longer use of NSAIDs
◽smoking
◽drinking alcohol

◽older age
◽poor health
◽advanced liver disease
◽bleeding problems

NSAIDs should only be used:
◽exactly as prescribed
◽at the lowest dose possible for your treatment
◽for the shortest time needed

What are NSAIDs?
NSAIDs are used to treat pain and redness, swelling, and heat (inflammation) from medical conditions such as different types of arthritis, menstrual cramps, and other types of short-term pain.

Who should not take NSAIDs?
Do not take NSAIDs:
◾if you have had an asthma attack, hives, or other allergic reaction with aspirin or any other NSAIDs.
◾right before or after heart bypass surgery.

Before taking NSAIDs, tell your healthcare provider about all of your medical conditions, including if you:
◾have liver or kidney problems
◾have high blood pressure
◾have asthma
◾are pregnant or plan to become pregnant. Taking NSAIDs at about 20 weeks of pregnancy or later may harm your unborn baby. If you need to take NSAIDs for more than 2 days when you are between 20 and 30 weeks of pregnancy, your healthcare provider may need to monitor the amount of fluid in your womb around your baby. You should not take NSAIDs after about 30 weeks of pregnancy.
◾are breastfeeding or plan to breast feed.

Tell your healthcare provider about all of the medicines you take, including prescription or over-the-counter medicines, vitamins or herbal supplements. NSAIDs and some other medicines can interact with each other and cause serious side effects. Do not start taking any new medicine without talking to your healthcare provider first.

What are the possible side effects of NSAIDs? NSAIDs can cause serious side effects, including: See "WHAT IS THE MOST IMPORTANT INFORMATION I SHOULD KNOW ABOUT MEDICINES CALLED NONSTEROIDAL ANTI-INFLAMMATORY DRUGS (NSAIDS)?"
◾new or worse high blood pressure
◾heart failure
◾liver problems including liver failure
◾kidney problems including kidney failure
◾low red blood cells (anemia)
◾life-threatening skin reactions
◾life-threatening allergic reactions
◾ Other side effects of NSAIDs include: stomach pain, constipation, diarrhea, gas, heartburn, nausea, vomiting, and dizziness.

Get emergency help right away if you get any of the following symptoms:

◾shortness of breath or trouble breathing
◾chest pain
◾weakness in one part or side of your body

◾slurred speech
◾swelling of the face or throat

Stop taking your NSAID and call your healthcare provider right away if you get any of the following symptoms:

◾nausea
◾more tired or weaker than usual
◾diarrhea
◾itching
◾your skin or eyes look yellow
◾indigestion or stomach pain
◾flu-like symptoms

◾vomit blood
◾there is blood in your bowel movement or it is black and sticky, like tar
◾unusual weight gain
◾skin rash or blisters with fever
◾swelling of the arms, legs, hands and feet

If you take too much of your NSAID, call your healthcare provider or get medical help right away.
These are not all the possible side effects of NSAIDs. For more information, ask your healthcare provider or pharmacist about NSAIDs.
Call your doctor for medical advice about side effects. You may report side effects to Dr. Reddy's Medical Information Department, at 1-888-375-3784 or FDA at 1-800-FDA-1088.

Other information about NSAIDs
◾Aspirin is an NSAID but it does not increase the chance of a heart attack. Aspirin can cause bleeding in the brain, stomach, and intestines. Aspirin can also cause ulcers in the stomach and intestines.
◾Some NSAIDs are sold in lower doses without a prescription (over-the-counter). Talk to your healthcare provider before using over-the-counter NSAIDs for more than 10 days.

General information about the safe and effective use of NSAIDs
Medicines are sometimes prescribed for purposes other than those listed in a Medication Guide. Do not use NSAIDs for a condition for which it was not prescribed. Do not give NSAIDs to other people, even if they have the same symptoms that you have. It may harm them.
If you would like more information about NSAIDs, talk with your healthcare provider. You can ask your pharmacist or healthcare provider for information about NSAIDs that is written for health professionals.

This Medication Guide has been approved by the U.S. Food and Drug Administration.

Manufactured by:
Aavis Pharmaceuticals
Hoschton, GA 30548
Code. L7049/00
Rev. 04/2022
Distributed by:
Dr Reddy's Laboratories Inc.
Princeton, NJ 08540 USA

Packaged and Distributed by:

MAJOR® PHARMACEUTICALS

Indianapolis, IN 46268 USA

Refer to package label for Distributor's NDC Number

Package/Label Display Panel

MAJOR®

NDC 0904-7303-04

Unit Dose

Ketorolac

Tromethamine

Tablets, USP

10 mg

Pharmacist: Dispense with

Medication Guide

30 TABLETS (3 x 10)

Rx only